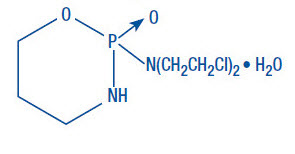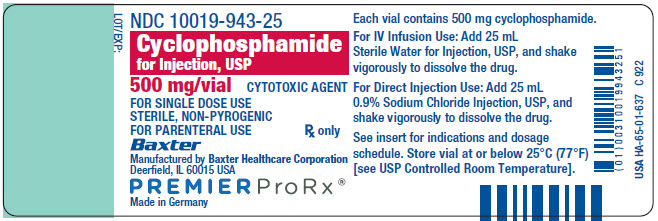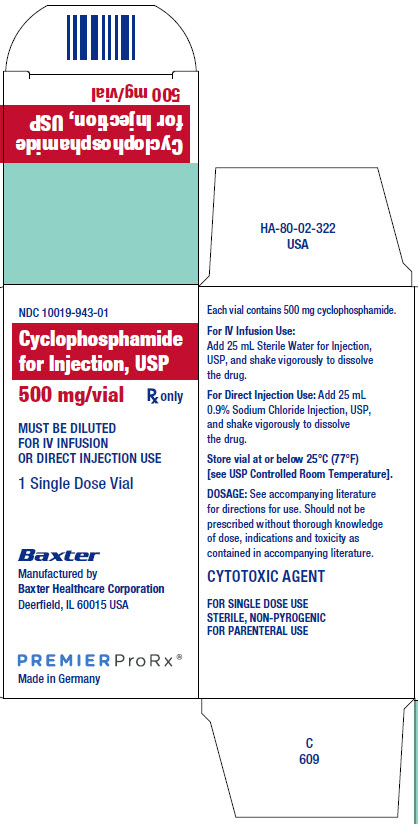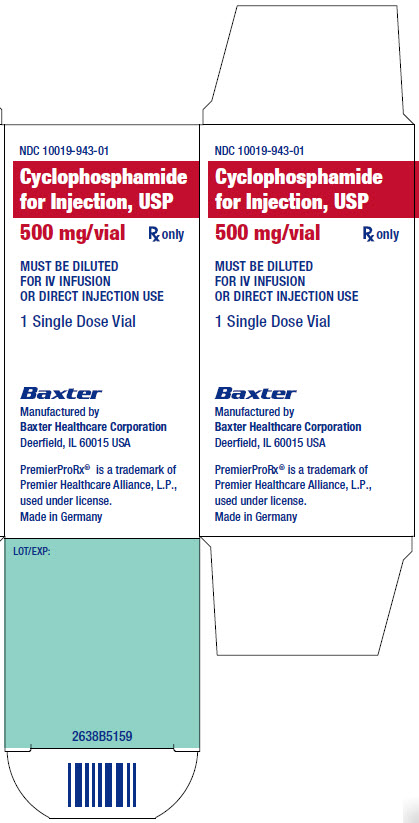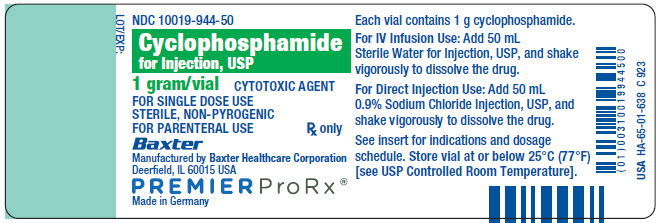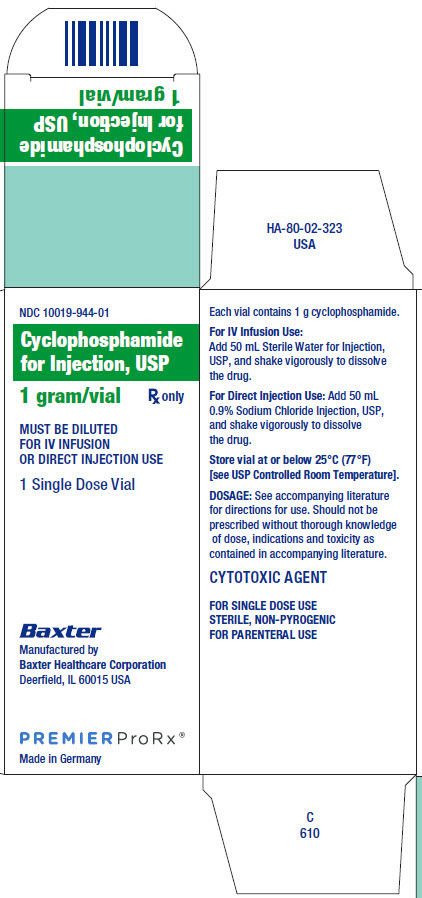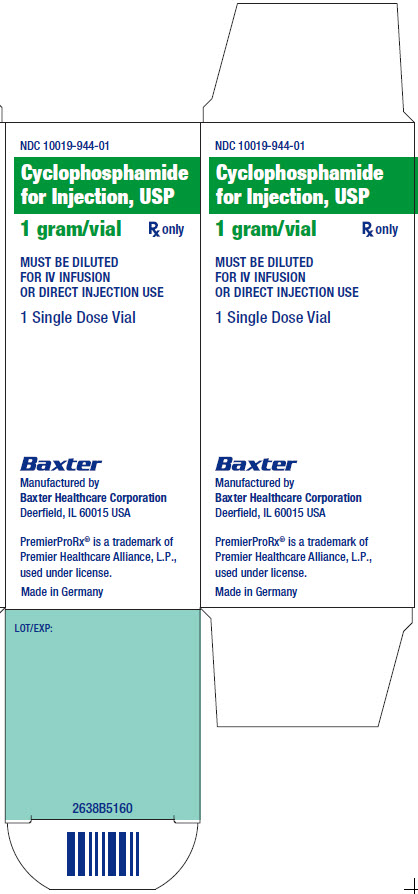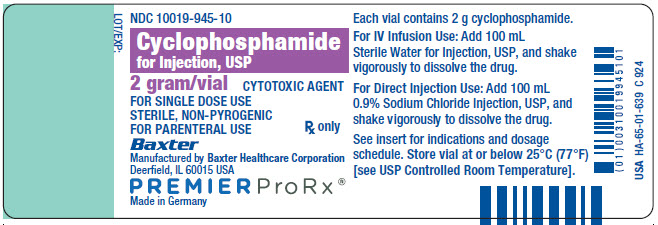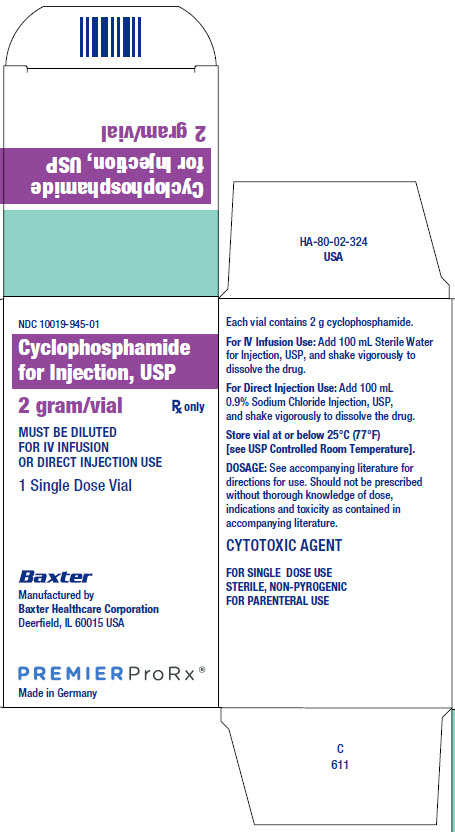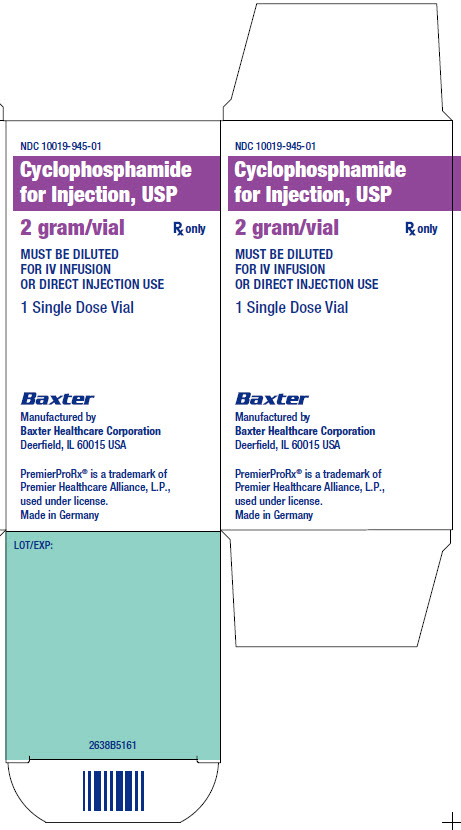 DRUG LABEL: CYCLOPHOSPHAMIDE
NDC: 83703-549 | Form: INJECTION, POWDER, FOR SOLUTION
Manufacturer: Bamboo US Bidco LCC
Category: prescription | Type: HUMAN PRESCRIPTION DRUG LABEL
Date: 20251203

ACTIVE INGREDIENTS: CYCLOPHOSPHAMIDE 500 mg/25 mL

HIGHLIGHTS OF PRESCRIBING INFORMATION

These highlights do not include all the information needed to use CYCLOPHOSPHAMIDE safely and effectively. See full prescribing information for CYCLOPHOSPHAMIDE.
CYCLOPHOSPHAMIDE for injection, for intravenous use
Initial U.S. Approval: 1959

1 INDICATIONS AND USAGE

Cyclophosphamide is an alkylating drug indicated for treatment of:

- Malignant Diseases: malignant lymphomas: Hodgkin’s disease, lymphocytic lymphoma, mixed-cell type lymphoma, histiocytic lymphoma, Burkitt’s lymphoma; multiple myeloma, leukemias, mycosis fungoides, neuroblastoma, adenocarcinoma of ovary, retinoblastoma, breast carcinoma (1.1)
- Minimal Change Nephrotic Syndrome in Pediatric Patients:
- biopsy proven minimal change nephrotic syndrome patients who failed to adequately respond to or are unable to tolerate adrenocorticosteroid therapy (1.2)
  Limitations of Use:
  The safety and effectiveness for the treatment of nephrotic syndrome in adults or other renal disease has not been established.

2 DOSAGE AND ADMINISTRATION

Malignant Diseases: Adult and Pediatric Patients(2.1)

- Intravenous: Initial course for patients with no hematologic deficiency: 40 mg per kg to 50 mg per kg in divided doses over 2 to 5 days. Other regimens include 10 mg per kg to 15 mg per kg given every 7 to 10 days or 3 mg per kg to 5 mg per kg twice weekly.
- Oral: Usually 1 mg per kg per day to 5 mg per kg per day for both initial and maintenance dosing.

Minimal Change Nephrotic Syndrome in Pediatric Patients(2.2)

- Recommended oral dose: 2 mg per kg daily for 8 to 12 weeks (maximum cumulative dose 168 mg per kg). Treatment beyond 90 days increases the probability of sterility in males.

3 DOSAGE FORMS AND STRENGTHS

- Injection, sterile white powder: 500 mg, 1 g, and 2 g (3)

4 CONTRAINDICATIONS

- Hypersensitivity to cyclophosphamide (4)
- Urinary outflow obstruction (4)

5 WARNINGS AND PRECAUTIONS

- Myelosuppression, Immunosuppression, Bone Marrow Failure and Infections – Severe immunosuppression may lead to serious and sometimes fatal infections. Close hematological monitoring is required. (5.1)
- Urinary Tract and Renal Toxicity – Hemorrhagic cystitis, pyelitis, ureteritis, and hematuria can occur. Exclude or correct any urinary tract obstructions prior to treatment. (5.2)
- Cardiotoxicity – Myocarditis, myopericarditis, pericardial effusion, arrhythmias and congestive heart failure, which may be fatal, have been reported. Monitor patients, especially those with risk factors for cardiotoxicity or pre-existing cardiac disease. (5.3)
- Pulmonary Toxicity – Pneumonitis, pulmonary fibrosis and pulmonary veno-occlusive disease leading to respiratory failure may occur. Monitor patients for signs and symptoms of pulmonary toxicity. (5.4)
- Secondary malignancies (5.5)
- Veno-occlusive Liver Disease - Fatal outcome can occur. (5.6)
- Embryo-Fetal Toxicity - Can cause fetal harm. Advise female patients of reproductive potential to avoid pregnancy. (5.7, 8.1, 8.6)

6 ADVERSE REACTIONS

Adverse reactions reported most often include neutropenia, febrile neutropenia, fever, alopecia, nausea, vomiting, and diarrhea. (6.1)

To report SUSPECTED ADVERSE REACTIONS, contact Baxter Healthcare at 1-866-888-2472 or FDA at 1-800-FDA-1088 or www.fda.gov/medwatch.

8 USE IN SPECIFIC POPULATIONS

- Nursing Mothers: Discontinue drug or nursing. (8.3)
- Females and males of reproductive potential: Counsel patients on pregnancy prevention and planning. (8.6)
- Renal Patients: Monitor for toxicity in patients with moderate and severe renal impairment. (8.7, 12.3)

FULL PRESCRIBING INFORMATION

1 INDICATIONS AND USAGE

1.1 Malignant Diseases

Cyclophosphamide is indicated for the treatment of:

- malignant lymphomas (Stages III and IV of the Ann Arbor staging system), Hodgkin’s disease, lymphocytic lymphoma (nodular or diffuse), mixed-cell type lymphoma, histiocytic lymphoma, Burkitt’s lymphoma
- multiple myeloma
- leukemias: Chronic lymphocytic leukemia, chronic granulocytic leukemia (it is usually ineffective in acute blastic crisis), acute myelogenous and monocytic leukemia, acute lymphoblastic (stem-cell) leukemia (cyclophosphamide given during remission is effective in prolonging its duration)
- mycosis fungoides (advanced disease)
- neuroblastoma (disseminated disease)
- adenocarcinoma of the ovary
- retinoblastoma
- carcinoma of the breast

Cyclophosphamide, although effective alone in susceptible malignancies, is more frequently used concurrently or sequentially with other antineoplastic drugs.

1.2 Minimal Change Nephrotic Syndrome in Pediatric Patients

Cyclophosphamide is indicated for the treatment of biopsy proven minimal change nephrotic syndrome in pediatrics patients who failed to adequately respond to or are unable to tolerate adrenocorticosteroid therapy.

Limitations of Use:
The safety and effectiveness for the treatment of nephrotic syndrome in adults or other renal disease has not been established.

2 DOSAGE AND ADMINISTRATION

During or immediately after the administration, adequate amounts of fluid should be ingested or infused to force diuresis in order to reduce the risk of urinary tract toxicity. Therefore, cyclophosphamide should be administered in the morning.

2.1 Dosing for Malignant Diseases

Adults and Pediatric Patients
Intravenous
When used as the only oncolytic drug therapy, the initial course of cyclophosphamide for patients with no hematologic deficiency usually consists of 40 mg per kg to 50 mg per kg given intravenously in divided doses over a period of 2 to 5 days. Other intravenous regimens include 10 mg per kg to 15 mg per kg given every 7 to 10 days or 3 mg per kg to 5 mg per kg twice weekly.

Oral
Oral cyclophosphamide dosing is usually in the range of 1 mg per kg per day to 5 mg per kg per day for both initial and maintenance dosing.

Many other regimens of intravenous and oral cyclophosphamide have been reported. Dosages must be adjusted in accord with evidence of antitumor activity and/or leukopenia. The total leukocyte count is a good, objective guide for regulating dosage.

When cyclophosphamide is included in combined cytotoxic regimens, it may be necessary to reduce the dose of cyclophosphamide as well as that of the other drugs.

2.2 Dosing for Minimal Change Nephrotic Syndrome in Pediatric Patients

An oral dose of 2 mg per kg daily for 8 to 12 weeks (maximum cumulative dose 168 mg per kg) is recommended. Treatment beyond 90 days increases the probability of sterility in males [see Use in Specific Populations (8.4)].

2.3 Preparation, Handling and Administration

Handle and dispose of cyclophosphamide in a manner consistent with other cytotoxic drugs. 1Caution should be exercised when handling and preparing Cyclophosphamide for Injection, USP. To minimize the risk of dermal exposure, always wear gloves when handling vials containing Cyclophosphamide for Injection, USP.

Cyclophosphamide for Injection, USP

Intravenous Administration

Parenteral drug products should be inspected visually for particulate matter and discoloration prior to administration, whenever solution and container permit. Do not use cyclophosphamide vials if there are signs of melting. Melted cyclophosphamide is a clear or yellowish viscous liquid usually found as a connected phase or in droplets in the affected vials.

Cyclophosphamide does not contain any antimicrobial preservative and thus care must be taken to assure the sterility of prepared solutions. Use aseptic technique.

For Direct Intravenous Injection

Reconstitute Cyclophosphamide with 0.9% Sodium Chloride Injection, USP only, using the volumes listed below in Table 1. Add the diluent to the vial and shake the vial vigorously to dissolve the drug completely. Do not use Sterile Water for Injection, USP because it results in a hypotonic solution and should not be injected directly.

Table 1: Reconstitution for Direct Intravenous Injection
Strength | Volume of 0.9% Sodium Chloride | Cyclophosphamide Concentration
500 mg | 25 mL | 20 mg per mL
1 g | 50 mL | 20 mg per mL
2 g | 100 mL | 20 mg per mL

For Intravenous Infusion

Reconstitution of Cyclophosphamide:
Reconstitute Cyclophosphamide using 0.9% Sodium Chloride Injection, USP or Sterile Water for Injection, USP with the volume of diluent listed below in Table 2. Add the diluent to the vial and shake the vial vigorously to dissolve the drug completely.

Table 2: Reconstitution in preparation for Intravenous Infusion
Strength | Volume of Diluent | Cyclophosphamide; Concentration
500 mg | 25 mL | 20 mg per mL
1 g | 50 mL | 20 mg per mL
2 g | 100 mL | 20 mg per mL

Dilution of Reconstituted Cyclophosphamide:
Further dilute the reconstituted Cyclophosphamide solution to a minimum concentration of 2 mg per mL with any of the following diluents:

-
  - 5% Dextrose Injection, USP
  - 5% Dextrose and 0.9% Sodium Chloride Injection, USP
  - 0.45% Sodium Chloride Injection, USP

To reduce the likelihood of adverse reactions that appear to be administration rate-dependent (e.g., facial swelling, headache, nasal congestion, scalp burning), cyclophosphamide should be injected or infused very slowly. Duration of the infusion also should be appropriate for the volume and type of carrier fluid to be infused.

Storage of Reconstituted and Diluted Cyclophosphamide Solution:

If not used immediately, for microbiological integrity, cyclophosphamide solutions should be stored as described in Table 3.

Table 3: Storage of Cyclophosphamide Solutions
Diluent | Storage
 | Room Temperature | Refrigerated
Reconstituted Solution(Without Further Dilution)
0.9% Sodium Chloride Injection, USP | up to 24 hrs | up to 6 days
Sterile Water for Injection, USP | Do not store; use immediately
Diluted Solutions [Storage time is the total time cyclophosphamide is in solution including the time it is reconstituted in 0.9% Sterile Sodium Chloride Injection, USP or Sterile Water for Injection, USP.]
0.45% Sodium Chloride Injection, USP | up to 24 hrs | up to 6 days
5% Dextrose Injection, USP | up to 24 hrs | up to 36 hrs
5% Dextrose and 0.9% Sodium Chloride Injection, USP | up to 24 hrs | up to 36 hrs

Use of Reconstituted Solution for Oral Administration

Liquid preparations of cyclophosphamide for oral administration may be prepared by dissolving cyclophosphamide for injection in Aromatic Elixir, National Formulary (NF). Such preparations should be stored under refrigeration in glass containers and used within 14 days.

3 DOSAGE FORMS AND STRENGTHS

Cyclophosphamide for Injection, USP is a sterile white powder available in

-
  - 500 mg
  - 1 g
  - 2 g

4 CONTRAINDICATIONS

- Hypersensitivity
  Cyclophosphamide is contraindicated in patients who have a history of severe hypersensitivity reactions to it, any of its metabolites, or to other components of the product. Anaphylactic reactions including death have been reported with cyclophosphamide. Possible cross-sensitivity with other alkylating agents can occur.
- Urinary Outflow Obstruction
  Cyclophosphamide is contraindicated in patients with urinary outflow obstruction [see Warnings and Precautions (5.2)].

5 WARNINGS AND PRECAUTIONS

5.1 Myelosuppression, Immunosuppression, Bone Marrow Failure and Infections

Cyclophosphamide can cause myelosuppression (leukopenia, neutropenia, thrombocytopenia and anemia), bone marrow failure, and severe immunosuppression which may lead to serious and sometimes fatal infections, including sepsis and septic shock. Latent infections can be reactivated [see Adverse Reactions (6.2)].

Antimicrobial prophylaxis may be indicated in certain cases of neutropenia at the discretion of the managing physician. In case of neutropenic fever, antibiotic therapy is indicated. Antimycotics and/or antivirals may also be indicated.

Monitoring of complete blood counts is essential during cyclophosphamide treatment so that the dose can be adjusted, if needed. Cyclophosphamide should not be administered to patients with neutrophils ≤1,500/mm^3and platelets < 50,000/mm^3. Cyclophosphamide treatment may not be indicated, or should be interrupted, or the dose reduced, in patients who have or who develop a serious infection. G-CSF may be administered to reduce the risks of neutropenia complications associated with cyclophosphamide use. Primary and secondary prophylaxis with G-CSF should be considered in all patients considered to be at increased risk for neutropenia complications. The nadirs of the reduction in leukocyte count and thrombocyte count are usually reached in weeks 1 and 2 of treatment. Peripheral blood cell counts are expected to normalize after approximately 20 days. Bone marrow failure has been reported. Severe myelosuppression may be expected particularly in patients pretreated with and/or receiving concomitant chemotherapy and/or radiation therapy.

5.2 Urinary Tract and Renal Toxicity

Hemorrhagic cystitis, pyelitis, ureteritis, and hematuria have been reported with cyclophosphamide. Medical and/or surgical supportive treatment may be required to treat protracted cases of severe hemorrhagic cystitis. Discontinue cyclophosphamide therapy in case of severe hemorrhagic cystitis. Urotoxicity (bladder ulceration, necrosis, fibrosis, contracture and secondary cancer) may require interruption of cyclophosphamide treatment or cystectomy. Urotoxicity can be fatal. Urotoxicity can occur with short-term or long-term use of cyclophosphamide.

Before starting treatment, exclude or correct any urinary tract obstructions [see Contraindications (4)]. Urinary sediment should be checked regularly for the presence of erythrocytes and other signs of urotoxicity and/or nephrotoxicity. Cyclophosphamide should be used with caution, if at all, in patients with active urinary tract infections. Aggressive hydration with forced diuresis and frequent bladder emptying can reduce the frequency and severity of bladder toxicity. Mesna has been used to prevent severe bladder toxicity.

5.3 Cardiotoxicity

Myocarditis, myopericarditis, pericardial effusion including cardiac tamponade, and congestive heart failure, which may be fatal, have been reported with cyclophosphamide therapy.

Supraventricular arrhythmias (including atrial fibrillation and flutter) and ventricular arrhythmias (including severe QT prolongation associated with ventricular tachyarrhythmia) have been reported after treatment with regimens that included cyclophosphamide.

The risk of cardiotoxicity may be increased with high doses of cyclophosphamide, in patients with advanced age, and in patients with previous radiation treatment to the cardiac region and/or previous or concomitant treatment with other cardiotoxic agents.

Particular caution is necessary in patients with risk factors for cardiotoxicity and in patients with pre-existing cardiac disease.

Monitor patients with risk factors for cardiotoxicity and with pre-existing cardiac disease.

5.4 Pulmonary Toxicity

Pneumonitis, pulmonary fibrosis, pulmonary veno-occlusive disease and other forms of pulmonary toxicity leading to respiratory failure have been reported during and following treatment with cyclophosphamide. Late onset pneumonitis (greater than 6 months after start of cyclophosphamide) appears to be associated with increased mortality. Pneumonitis may develop years after treatment with cyclophosphamide.

Monitor patients for signs and symptoms of pulmonary toxicity.

5.5 Secondary Malignancies

Cyclophosphamide is genotoxic [see Nonclinical Toxicology(13.1)]. Secondary malignancies (urinary tract cancer, myelodysplasia, acute leukemias, lymphomas, thyroid cancer, and sarcomas) have been reported in patients treated with cyclophosphamide-containing regimens .The risk of bladder cancer may be reduced by prevention of hemorrhagic cystitis.

5.6 Veno-occlusive Liver Disease

Veno-occlusive liver disease (VOD) including fatal outcome has been reported in patients receiving cyclophosphamide-containing regimens. A cytoreductive regimen in preparation for bone marrow transplantation that consists of cyclophosphamide in combination with whole-body irradiation, busulfan, or other agents has been identified as a major risk factor. VOD has also been reported to develop gradually in patients receiving long-term low-dose immunosuppressive doses of cyclophosphamide. Other risk factors predisposing to the development of VOD include preexisting disturbances of hepatic function, previous radiation therapy of the abdomen, and a low performance status.

5.7 Embryo-Fetal Toxicity

Cyclophosphamide can cause fetal harm when administered to a pregnant woman [see Use in Specific Populations (8.1)]. Exposure to cyclophosphamide during pregnancy may cause birth defects, miscarriage, fetal growth retardation, and fetotoxic effects in the newborn. Cyclophosphamide is teratogenic and embryo-fetal toxic in mice, rats, rabbits and monkeys.

Advise female patients of reproductive potential to avoid becoming pregnant and to use highly effective contraception during treatment and for up to 1 year after completion of therapy [see Use in Specific Populations (8.6)].

5.8 Infertility

Male and female reproductive function and fertility may be impaired in patients being treated with cyclophosphamide. Cyclophosphamide interferes with oogenesis and spermatogenesis. It may cause sterility in both sexes. Development of sterility appears to depend on the dose of cyclophosphamide, duration of therapy, and the state of gonadal function at the time of treatment. Cyclophosphamide-induced sterility may be irreversible in some patients. Advise patients on the potential risks for infertility [see Use in Specific Populations(8.4and 8.6)].

5.9 Impairment of Wound Healing

Cyclophosphamide may interfere with normal wound healing.

5.10 Hyponatremia

Hyponatremia associated with increased total body water, acute water intoxication, and a syndrome resembling SIADH (syndrome of inappropriate secretion of antidiuretic hormone), which may be fatal, has been reported.

6 ADVERSE REACTIONS

The following adverse reactions are discussed in more detail in other sections of the labeling.

- Hypersensitivity [see Contraindications (4)]
- Myelosuppression, Immunosuppression, Bone Marrow Failure, and Infections [see Warnings and Precautions (5.1)]
- Urinary Tract and Renal Toxicity [see Warnings and Precautions (5.2)]
- Cardiotoxicity [see Warnings and Precautions (5.3)]
- Pulmonary Toxicity [see Warnings and Precautions (5.4)]
- Secondary Malignancies [see Warnings and Precautions (5.5)]
- Veno-occlusive Liver Disease [see Warnings and Precautions (5.6)]
- Embryo-Fetal Toxicity [see Warnings and Precautions (5.7)]
- Reproductive System Toxicity [see Warnings and Precautions (5.8)and Use in Specific Populations(8.4and 8.6)]
- Impaired Wound Healing [see Warnings and Precautions (5.9)]
- Hyponatremia [see Warnings and Precautions (5.10)]

6.1 Common Adverse Reactions

Hematopoietic system:
Neutropenia occurs in patients treated with cyclophosphamide. The degree of neutropenia is particularly important because it correlates with a reduction in resistance to infections. Fever without documented infection has been reported in neutropenic patients.

Gastrointestinal system:
Nausea and vomiting occur with cyclophosphamide therapy. Anorexia and, less frequently, abdominal discomfort or pain and diarrhea may occur. There are isolated reports of hemorrhagic colitis, oral mucosal ulceration and jaundice occurring during therapy.

Skin and its structures:
Alopecia occurs in patients treated with cyclophosphamide. Skin rash occurs occasionally in patients receiving the drug. Pigmentation of the skin and changes in nails can occur.

6.2 Postmarketing Experience

The following adverse reactions have been identified from clinical trials or post-marketing surveillance. Because they are reported from a population from unknown size, precise estimates of frequency cannot be made.

Cardiac:cardiac arrest, ventricular fibrillation, ventricular tachycardia, cardiogenic shock, pericardial effusion (progressing to cardiac tamponade), myocardial hemorrhage, myocardial infarction, cardiac failure (including fatal outcomes), cardiomyopathy, myocarditis, pericarditis, carditis, atrial fibrillation, supraventricular arrhythmia, ventricular arrhythmia, bradycardia, tachycardia, palpitations, QT prolongation.

Congenital, Familial and Genetic: intra-uterine death, fetal malformation, fetal growth retardation, fetal toxicity (including myelosuppression, gastroenteritis).

Ear and Labyrinth:deafness, hearing impaired, tinnitus.

Endocrine:water intoxication.

Eye:visual impairment, conjunctivitis, lacrimation.

Gastrointestinal:gastrointestinal hemorrhage, acute pancreatitis, colitis, enteritis, cecitis, stomatitis, constipation, parotid gland inflammation.

General Disorders and Administrative Site Conditions:multiorgan failure, general physical deterioration, influenza-like illness, injection/infusion site reactions (thrombosis, necrosis, phlebitis, inflammation, pain, swelling, erythema), pyrexia, edema, chest pain, mucosal inflammation, asthenia, pain, chills, fatigue, malaise, headache.

Hematologic:myelosuppression, bone marrow failure, disseminated intravascular coagulation and hemolytic uremic syndrome (with thrombotic microangiopathy).

Hepatic:veno-occlusive liver disease, cholestatic hepatitis, cytolytic hepatitis, hepatitis, cholestasis; hepatotoxicity with hepatic failure, hepatic encephalopathy, ascites, hepatomegaly, blood bilirubin increased, hepatic function abnormal, hepatic enzymes increased.

Immune:immunosuppression, anaphylactic shock and hypersensitivity reaction.

Infections:The following manifestations have been associated with myelosuppression and immunosuppression caused by cyclophosphamide: increased risk for and severity of pneumonias (including fatal outcomes), other bacterial, fungal, viral, protozoal and, parasitic infections; reactivation of latent infections, (including viral hepatitis, tuberculosis), Pneumocystis jiroveci, herpes zoster, Strongyloides, sepsis and septic shock.

Investigations:blood lactate dehydrogenase increased, C-reactive protein increased.

Metabolism and Nutrition:hyponatremia, fluid retention, blood glucose increased, blood glucose decreased.

Musculoskeletal and Connective Tissue: rhabdomyolysis, scleroderma, muscle spasms, myalgia, arthralgia.

Neoplasms:acute leukemia, myelodysplastic syndrome, lymphoma, sarcomas, renal cell carcinoma, renal pelvis cancer, bladder cancer, ureteric cancer, thyroid cancer.

Nervous System:encephalopathy, convulsion, dizziness, neurotoxicity has been reported and manifested as reversible posterior leukoencephalopathy syndrome, myelopathy, peripheral neuropathy, polyneuropathy, neuralgia, dysesthesia, hypoesthesia, paresthesia, tremor, dysgeusia, hypogeusia, parosmia.

Pregnancy:premature labor.

Psychiatric:confusional state.

Renal and Urinary:renal failure, renal tubular disorder, renal impairment, nephropathy toxic, hemorrhagic cystitis, bladder necrosis, cystitis ulcerative, bladder contracture, hematuria, nephrogenic diabetes insipidus, atypical urinary bladder epithelial cells.

Reproductive System:infertility, ovarian failure, ovarian disorder, amenorrhea, oligomenorrhea, testicular atrophy, azoospermia, oligospermia.

Respiratory:pulmonary veno-occlusive disease, acute respiratory distress syndrome, interstitial lung disease as manifested by respiratory failure (including fatal outcomes), obliterative bronchiolitis, organizing pneumonia, alveolitis allergic, pneumonitis, pulmonary hemorrhage; respiratory distress, pulmonary hypertension, pulmonary edema, pleural effusion, bronchospasm, dyspnea, hypoxia, cough, nasal congestion, nasal discomfort, oropharyngeal pain, rhinorrhea.

Skin and Subcutaneous Tissue:toxic epidermal necrolysis, Stevens-Johnson syndrome, erythema multiforme, palmar-plantar erythrodysesthesia syndrome, radiation recall dermatitis, toxic skin eruption, urticaria, dermatitis, blister, pruritus, erythema, nail disorder, facial swelling, hyperhidrosis.

Tumor lysis syndrome:like other cytotoxic drugs, cyclophosphamide may induce tumor-lysis syndrome and hyperuricemia in patients with rapidly growing tumors.

Vascular:pulmonary embolism, venous thrombosis, vasculitis, peripheral ischemia, hypertension, hypotension, flushing, hot flush.

7 DRUG INTERACTIONS

Cyclophosphamide is a pro-drug that is activated by cytochrome P450s [see Clinical Pharmacology (12.3)].

An increase of the concentration of cytotoxic metabolites may occur with:

- Protease inhibitors: Concomitant use of protease inhibitors may increase the concentration of cytotoxic metabolites. Use of protease inhibitor-based regimens was found to be associated with a higher incidence of infections and neutropenia in patients receiving cyclophosphamide, doxorubicin, and etoposide (CDE) than use of a Non-Nucleoside Reverse Transcriptase Inhibitor-based regimen.

Combined or sequential use of cyclophosphamide and other agents with similar toxicities can potentiate toxicities.

- Increased hematotoxicity and/or immunosuppression may result from a combined effect of cyclophosphamide and, for example:
  - ACE inhibitors: ACE inhibitors can cause leukopenia.
  - Natalizumab
  - Paclitaxel: Increased hematotoxicity has been reported when cyclophosphamide was administered after paclitaxel infusion.
  - Thiazide diuretics
  - Zidovudine
- Increased cardiotoxicity may result from a combined effect of cyclophosphamide and, for example:
  - Anthracyclines
  - Cytarabine
  - Pentostatin
  - Radiation therapy of the cardiac region
  - Trastuzumab
- Increased pulmonary toxicity may result from a combined effect of cyclophosphamide and, for example:
  - Amiodarone
  - G-CSF, GM-CSF (granulocyte colony-stimulating factor, granulocyte macrophage colony-stimulating factor): Reports suggest an increased risk of pulmonary toxicity in patients treated with cytotoxic chemotherapy that includes cyclophosphamide and G-CSF or GMCSF.
- Increased nephrotoxicity may result from a combined effect of cyclophosphamide and, for example:
  - Amphotericin B
  - Indomethacin: Acute water intoxication has been reported with concomitant use of indomethacin
- Increase in other toxicities:
  - Azathioprine: Increased risk of hepatotoxicity (liver necrosis)
  - Busulfan: Increased incidence of hepatic veno-occlusive disease and mucositis has been reported.
  - Protease inhibitors: Increased incidence of mucositis
- Increased risk of hemorrhagic cystitis may result from a combined effect of cyclophosphamide and past or concomitant radiation treatment.

Etanercept: In patients with Wegener’s granulomatosis, the addition of etanercept to standard treatment, including cyclophosphamide, was associated with a higher incidence of non-cutaneous malignant solid tumors.

Metronidazole: Acute encephalopathy has been reported in a patient receiving cyclophosphamide and metronidazole. Causal association is unclear. In an animal study, the combination of cyclophosphamide with metronidazole was associated with increased cyclophosphamide toxicity.

Tamoxifen: Concomitant use of tamoxifen and chemotherapy may increase the risk of thromboembolic complications.

Coumarins: Both increased and decreased warfarin effect have been reported in patients receiving warfarin and cyclophosphamide.

Cyclosporine: Lower serum concentrations of cyclosporine have been observed in patients receiving a combination of cyclophosphamide and cyclosporine than in patients receiving only cyclosporine. This interaction may result in an increased incidence of graft-versus-host disease.

Depolarizing muscle relaxants: Cyclophosphamide treatment causes a marked and persistent inhibition of cholinesterase activity. Prolonged apnea may occur with concurrent depolarizing muscle relaxants (e.g., succinylcholine). If a patient has been treated with cyclophosphamide within 10 days of general anesthesia, alert the anesthesiologist.

8 USE IN SPECIFIC POPULATIONS

8.1 Pregnancy

Pregnancy Category D

Risk Summary
Cyclophosphamide can cause fetal harm when administered to a pregnant woman based on its mechanism of action and published reports of effects in pregnant patients or animals. Exposure to cyclophosphamide during pregnancy may cause fetal malformations, miscarriage, fetal growth retardation, and toxic effects in the newborn. Cyclophosphamide is teratogenic and embryo-fetal toxic in mice, rats, rabbits and monkeys. If this drug is used during pregnancy, or if the patient becomes pregnant while taking this drug, apprise the patient of the potential hazard to a fetus.

Human Data
Malformations of the skeleton, palate, limbs and eyes as well as miscarriage have been reported after exposure to cyclophosphamide in the first trimester. Fetal growth retardation and toxic effects manifesting in the newborn, including leukopenia, anemia, pancytopenia, severe bone marrow hypoplasia, and gastroenteritis have been reported after exposure to cyclophosphamide.

Animal Data
Administration of cyclophosphamide to pregnant mice, rats, rabbits and monkeys during the period of organogenesis at doses at or below the dose in patients based on body surface area resulted in various malformations, which included neural tube defects, limb and digit defects and other skeletal anomalies, cleft lip and palate, and reduced skeletal ossification.

8.3 Nursing Mothers

Cyclophosphamide is present in breast milk. Neutropenia, thrombocytopenia, low hemoglobin, and diarrhea have been reported in infants breast fed by women treated with cyclophosphamide. Because of the potential for serious adverse reactions in nursing infants from cyclophosphamide, a decision should be made whether to discontinue nursing or to discontinue the drug, taking into account the importance of the drug to the mother.

8.4 Pediatric Use

Pre-pubescent girls treated with cyclophosphamide generally develop secondary sexual characteristics normally and have regular menses. Ovarian fibrosis with apparently complete loss of germ cells after prolonged cyclophosphamide treatment in late pre-pubescence has been reported. Girls treated with cyclophosphamide who have retained ovarian function after completing treatment are at increased risk of developing premature menopause.

Pre-pubescent boys treated with cyclophosphamide develop secondary sexual characteristics normally, but may have oligospermia or azoospermia and increased gonadotropin secretion. Some degree of testicular atrophy may occur. Cyclophosphamide-induced azoospermia is reversible in some patients, though the reversibility may not occur for several years after cessation of therapy.

8.5 Geriatric Use

There is insufficient data from clinical studies of cyclophosphamide available for patients 65 years of age and older to determine whether they respond differently than younger patients. In general, dose selection for an elderly patient should be cautious, usually starting at the low end of the dosing range, reflecting the greater frequency of decreased hepatic, renal, or cardiac functioning, and of concomitant disease or other drug therapy.

8.6 Females and Males of Reproductive Potential

Contraception
Pregnancy should be avoided during treatment with cyclophosphamide because of the risk of fetal harm [see Use in Specific Populations (8.1)] .

Female patients of reproductive potential should use highly effective contraception during and for up to 1 year after completion of treatment.

Male patients who are sexually active with female partners who are or may become pregnant should use a condom during and for at least 4 months after treatment.

Infertility
Females
Amenorrhea, transient or permanent, associated with decreased estrogen and increased gonadotropin secretion develops in a proportion of women treated with cyclophosphamide. Affected patients generally resume regular menses within a few months after cessation of therapy. The risk of premature menopause with cyclophosphamide increases with age. Oligomenorrhea has also been reported in association with cyclophosphamide treatment.

Animal data suggest an increased risk of failed pregnancy and malformations may persist after discontinuation of cyclophosphamide as long as oocytes/follicles exist that were exposed to cyclophosphamide during any of their maturation phases. The exact duration of follicular development in humans is not known, but may be longer than 12 months [see Nonclinical Toxicology (13.1)].

Males
Men treated with cyclophosphamide may develop oligospermia or azoospermia which are normally associated with increased gonadotropin but normal testosterone secretion.

8.7 Use in Patients with Renal Impairment

In patients with severe renal impairment, decreased renal excretion may result in increased plasma levels of cyclophosphamide and its metabolites. This may result in increased toxicity [see Clinical Pharmacology (12.3)]. Monitor patients with severe renal impairment (CrCl =10 mL/min to 24 mL/min) for signs and symptoms of toxicity.

Cyclophosphamide and its metabolites are dialyzable although there are probably quantitative differences depending upon the dialysis system being used. In patients requiring dialysis, use of a consistent interval between cyclophosphamide administration and dialysis should be considered.

8.8 Use in Patients with Hepatic Impairment

Patients with severe hepatic impairment have reduced conversion of cyclophosphamide to the active 4-hydroxyl metabolite, potentially reducing efficacy [see Clinical Pharmacology (12.3)].

10 OVERDOSAGE

No specific antidote for cyclophosphamide is known.

Overdosage should be managed with supportive measures, including appropriate treatment for any concurrent infection, myelosuppression, or cardiac toxicity should it occur.

Serious consequences of overdosage include manifestations of dose dependent toxicities such as myelosuppression, urotoxicity, cardiotoxicity (including cardiac failure), veno-occlusive hepatic disease, and stomatitis [see Warnings and Precautions(5.1, 5.2, 5.3and 5.6)] .

Patients who received an overdose should be closely monitored for the development of toxicities, and hematologic toxicity in particular.

Cyclophosphamide and its metabolites are dialyzable. Therefore, rapid hemodialysis is indicated when treating any suicidal or accidental overdose or intoxication.

Cystitis prophylaxis with mesna may be helpful in preventing or limiting urotoxic effects with cyclophosphamide overdose.

11 DESCRIPTION

Cyclophosphamide is a synthetic antineoplastic drug chemically related to the nitrogen mustards. The chemical name for cyclophosphamide is 2-[bis(2-chloroethyl)amino]tetrahydro-2H-1,3,2-oxazaphosphorine 2-oxide monohydrate, and has the following structural formula:

Cyclophosphamide is a white crystalline powder with the molecular formula C7H15Cl2N2O2P•H2O and a molecular weight of 279.1. Cyclophosphamide is soluble in water, saline, or ethanol.

Cyclophosphamide for Injection, USP is a sterile white powder available as 500 mg, 1 g, and 2 g strength vials.

- 500 mg vial contains 534.5 mg cyclophosphamide monohydrate equivalent to 500 mg cyclophosphamide
- 1 g vial contains 1069.0 mg cyclophosphamide monohydrate equivalent to 1 g cyclophosphamide
- 2 g vial contains 2138.0 mg cyclophosphamide monohydrate equivalent to 2 g cyclophosphamide

12 CLINICAL PHARMACOLOGY

12.1 Mechanism of Action

The mechanism of action is thought to involve cross-linking of tumor cell DNA.

12.2 Pharmacodynamics

Cyclophosphamide is biotransformed principally in the liver to active alkylating metabolites by a mixed function microsomal oxidase system. These metabolites interfere with the growth of susceptible rapidly proliferating malignant cells.

12.3 Pharmacokinetics

Following IV administration, elimination half-life (t1/2) ranges from 3 to 12 hours with total body clearance (CL) values of 4 to 5.6 L/h. Pharmacokinetics are linear over the dose range used clinically. When cyclophosphamide was administered at 4.0 g/m^2over a 90 minutes infusion, saturable elimination in parallel with first-order renal elimination describe the kinetics of the drug.

Absorption
After oral administration, peak concentrations of cyclophosphamide occurred at one hour. Area under the curve ratio for the drug after oral and IV administration (AUCpo: AUCiv) ranged from 0.87 to 0.96.

Distribution
Approximately 20% of cyclophosphamide is protein bound, with no dose dependent changes. Some metabolites are protein bound to an extent greater than 60%. Volume of distribution approximates total body water (30 to 50 L).

Metabolism
The liver is the major site of cyclophosphamide activation. Approximately 75% of the administered dose of cyclophosphamide is activated by hepatic microsomal cytochrome P450s including CYP2A6, 2B6, 3A4, 3A5, 2C9, 2C18 and 2C19, with 2B6 displaying the highest 4-hydroxylase activity. Cyclophosphamide is activated to form 4-hydroxycyclophosphamide, which is in equilibrium with its ring-open tautomer aldophosphamide. 4-hydroxycyclophosphamide and aldophosphamide can undergo oxidation by aldehyde dehydrogenases to form the inactive metabolites 4-ketocyclophosphamide and carboxyphosphamide, respectively. Aldophosphamide can undergo β-elimination to form active metabolites phosphoramide mustard and acrolein. This spontaneous conversion can be catalyzed by albumin and other proteins. Less than 5% of cyclophosphamide may be directly detoxified by side chain oxidation, leading to the formation of inactive metabolites 2-dechloroethylcyclophosphamide. At high doses, the fraction of parent compound cleared by 4-hydroxylation is reduced resulting in non-linear elimination of cyclophosphamide in patients. Cyclophosphamide appears to induce its own metabolism. Auto-induction results in an increase in the total clearance, increased formation of 4-hydroxyl metabolites and shortened t1/2values following repeated administration at 12- to 24-hour interval.

Elimination
Cyclophosphamide is primarily excreted as metabolites. 10 to 20% is excreted unchanged in the urine and 4% is excreted in the bile following IV administration.

Special Populations

Renal Impairment
The pharmacokinetics of cyclophosphamide were determined following one-hour intravenous infusion to renally impaired patients. The results demonstrated that the systemic exposure to cyclophosphamide increased as the renal function decreased. Mean dose-corrected AUC increased by 38% in the moderate renal group, (Creatinine clearance (CrCl of 25 to 50 mL/min), by 64% in the severe renal group (CrCl of 10 to 24 mL/min) and by 23% in the hemodialysis group (CrCl of < 10 mL/min) compared to the control group. The increase in exposure was significant in the severe group (p>0.05); thus, patients with severe renal impairment should be closely monitored for toxicity [see Use in Specific Populations (8.7)].

The dialyzability of cyclophosphamide was investigated in four patients on long-term hemodialysis. Dialysis clearance calculated by arterial-venous difference and actual drug recovery in dialysate averaged 104 mL/min, which is in the range of the metabolic clearance of 95 mL/min for the drug. A mean of 37% of the administered dose of cyclophosphamide was removed during hemodialysis. The elimination half-life (t1/2) was 3.3 hours in patients during hemodialysis, a 49% reduction of the 6.5 hours to t1/2reported in uremic patients. Reduction in t1/2, larger dialysis clearance than metabolic clearance, high extraction efficiency, and significant drug removal during dialysis, suggest that cyclophosphamide is dialyzable.

Hepatic Impairment
Total body clearance (CL) of cyclophosphamide is decreased by 40% in patients with severe hepatic impairment and elimination half-life (t1/2) is prolonged by 64%. Mean CL and t1/2were 45 ± 8.6 L/kg and 12.5 ± 1.0 hours respectively, in patients with severe hepatic impairment and 63 ± 7.6 L/kg and 7.6 ± 1.4 hours respectively in the control group [see Use in Specific Populations (8.8)].

13 NONCLINICAL TOXICOLOGY

13.1 Carcinogenesis, Mutagenesis, Impairment of Fertility

Cyclophosphamide administered by different routes, including intravenous, subcutaneous or intraperitoneal injection, or in drinking water, caused tumors in both mice and rats. In addition to leukemia and lymphoma, benign and malignant tumors were found at various tissue sites, including urinary bladder, mammary gland, lung, liver, and injection site [see Warnings and Precautions (5.5)].

Cyclophosphamide was mutagenic and clastogenic in multiple in vitroand in vivogenetic toxicology studies.

Cyclophosphamide is genotoxic in male and female germ cells. Animal data indicate that exposure of oocytes to cyclophosphamide during follicular development may result in a decreased rate of implantations and viable pregnancies, and in an increased risk of malformations. Male mice and rats treated with cyclophosphamide show alterations in male reproductive organs (e.g., decreased weights, atrophy, changes in spermatogenesis), and decreases in reproductive potential (e.g., decreased implantations and increased post-implantation loss) and increases in fetal malformations when mated with untreated females [see Use in Specific Populations (8.6)].

15 REFERENCES

1. OSHA Hazardous Drugs. OSHA. http://www.osha.gov/SLTC/hazardousdrugs/index.html.

16 HOW SUPPLIED/STORAGE AND HANDLING

Cyclophosphamide for Injection, USP is a sterile white powder containing cyclophosphamide and is supplied in vials for single dose use.

Cyclophosphamide for Injection, USP

1. NDC 10019-943-01 500 mg vial, carton of 1
2. NDC 10019-944-01 1 g vial, carton of 1
3. NDC 10019-945-01 2 g vial, carton of 1

Store vials at or below 25°C (77°F). During transport or storage of cyclophosphamide vials, temperature influences can lead to melting of the active ingredient, cyclophosphamide, [see Dosage and Administration (2.3)].

Cyclophosphamide is an antineoplastic product. Follow special handling and disposal procedures. 1

17 PATIENT COUNSELING INFORMATION

Advise the patient of the following:

- Inform patients of the possibility of myelosuppression, immunosuppression, and infections. Explain the need for routine blood cell counts. Instruct patients to monitor their temperature frequently and immediately report any occurrence of fever [see Warnings and Precautions (5.1)].
- Advise the patient to report urinary symptoms (patients should report if their urine has turned a pink or red color) and the need for increasing fluid intake and frequent voiding [see Warnings and Precautions (5.2)] .
- Advise patients to contact a healthcare professional immediately for any of the following: new onset or worsening shortness of breath, cough, swelling of the ankles/legs, palpitations, weight gain of more than 5 pounds in 24 hours, dizziness or loss of consciousness [see Warnings and Precautions (5.3)].
- Warn patients of the possibility of developing non-infectious pneumonitis. Advise patients to report promptly any new or worsening respiratory symptoms [see Warnings and Precautions (5.4)].
- Advise female patients of reproductive potential to use highly effective contraception during treatment and for up to 1 year after completion of therapy. There is a potential for harm to a fetus if a patient becomes pregnant during this period. Patients should immediately contact their healthcare provider if they become pregnant or if pregnancy is suspected during this period [see Warnings and Precautions (5.7)and Use in Specific Populations (8.1)].
- Advise male patients who are sexually active with a female partner who is or may become pregnant to use condoms during treatment and for up to 4 months after completion of therapy. There is a potential for harm to a fetus if a patient fathers a child during this period. Patients should immediately contact their healthcare provider if their female partner becomes pregnant or if pregnancy is suspected during this period [see Warnings and Precautions (5.7)and Use in Specific Populations (8.1)].
- Advise nursing mothers treated with cyclophosphamide to discontinue nursing or discontinue cyclophosphamide, taking into account the importance of the drug to the mother [see Use in Specific Populations (8.3)] .
- Explain to patients that side effects such as nausea, vomiting, stomatitis, impaired wound healing, amenorrhea, premature menopause, sterility and hair loss may be associated with cyclophosphamide administration. Other undesirable effects (including, e.g., dizziness, blurred vision, visual impairment) could affect the ability to drive or use machines [see Adverse Reactions(6.1and 6.2)].

Manufactured by:
Baxter Healthcare Corporation
Deerfield, IL 60015 USA

Product Made in Germany

PREMIERProRx®

For Product Inquiry 1 800 ANA DRUG (1-800-262-3784)

Baxter is a trademark of Baxter International Inc.
PREMIERProRx® is a trademark of Premier Healthcare Alliance, L.P., used under license.

HA-30-01-686

Revised March 2017

PACKAGE/LABEL PRINCIPAL DISPLAY PANEL

NDC 10019-943-25

C yclophosphamide
for Injection, USP

500 mg/vial

CYTOTOXIC AGENT

FOR SINGLE DOSE USE
STERILE, NON-PYROGENIC
FOR PARENTERAL USE

Baxter Logo

Manufactured by Baxter Healthcare Corporation
Deerfield, IL 60015 USA

PREMIER Pro Rx Logo
Made in Germany

LOT/EXP:

Each vial contains 500 mg cyclophosphamide.

For IV Infusion Use:Add 25 mL

Sterile Water for Injection, USP, and shake

vigorously to dissolve the drug.

For Direct Injection Use:Add 25 mL

0.9% Sodium Chloride Injection, USP, and

shake vigorously to dissolve the drug.

See insert for indications and dosage

schedule. Store vial at or below 25°C (77°F)

[see USP Controlled Room Temperature].

Bar Code
(01)00310019943251

USA HA-65-01-637 C922

NDC 10019-943-01

C yclophosphamide
for Injection, USP

500 mg/vial

Rx only

MUST BE DILUTED

FOR IV INFUSION

OR DIRECT INJECTION USE

1 Single Dose Vial

Baxter Logo

Manufactured by
Baxter Healthcare Corporation
Deerfield, IL 60015 USA

PREMIER Pro RxLogo
Made in Germany

C yclophosphamide
for Injection, USP

500 mg/vial

Barcode

HA-80-02-322
USA

Each vial contains 500 mg cyclophosphamide.

For IV Infusion Use:

Add 25 mL Sterile Water for Injection,

USP, and shake vigorously to dissolve

the drug.

For Direct Injection Use:Add 25 mL

0.9% Sodium Chloride Injection, USP,

and shake vigorously to dissolve

the drug.

Store vial at or below 25°C (77°F)

[ see USP Controlled Room Temperature].

DOSAGE:See accompanying literature

for directions for use. Should not be

prescribed without thorough knowledge

of dose, indications and toxicity as

contained in accompanying literature.

CYTOTOXIC AGENT

FOR SINGLE DOSE USE

STERILE, NON-PYROGENIC

FOR PARENTERAL USE

C
609

NDC 10019-943-01

C yclophosphamide
for Injection, USP

500 mg/vial

Rx only

MUST BE DILUTED

FOR IV INFUSION

OR DIRECT INJECTION USE

1 Single Dose Vial

Baxter Logo
Manufactured by
Baxter Healthcare Corporation
Deerfield, IL 60015 USA

PremierProRx is a trademark of

Premier Healthcare Alliance, L.P.,
used under license.
Made in Germany

LOT/EXP:

2638B5159

Barcode

NDC 10019-943-01

C yclophosphamide
for Injection, USP

500 mg/vial

Rx only

MUST BE DILUTED

FOR IV INFUSION

OR DIRECT INJECTION USE

1 Single Dose Vial

Baxter Logo
Manufactured by
Baxter Healthcare Corporation
Deerfield, IL 60015 USA

PremierProRx is a trademark of

Premier Healthcare Alliance, L.P.,
used under license.
Made in Germany

NDC 10019-944-50

C yclophosphamide
for Injection, USP

1 gram/vial

CYTOTOXIC AGENT

FOR SINGLE DOSE USE
STERILE, NON-PYROGENIC
FOR PARENTERAL USE

Rx only

Baxter Logo
Manufactured by Baxter Healthcare Corporation
Deerfield, IL 60015 USA

PREMIER Pro Rx Logo
Made in Germany

LOT/EXP:

Each vial contains 1 gram cyclophosphamide.

For IV Infusion Use:Add 50 mL

Sterile Water for Injection, USP, and shake

vigorously to dissolve the drug.

For Direct Injection Use:Add 50 mL

0.9% Sodium Chloride Injection, USP, and

shake vigorously to dissolve the drug.

See insert for indications and dosage

schedule. Store vial at or below 25°C (77°F)

[see USP Controlled Room Temperature].

Bar Code
(01)00310019944500

USA HA-65-01-638 C 923

NDC 10019-944-01

C yclophosphamide
for Injection, USP

1 gram/vial

Rx only

MUST BE DILUTED

FOR IV INFUSION

OR DIRECT INJECTION USE

1 Single Dose Vial

Baxter Logo
Manufactured by
Baxter Healthcare Corporation
Deerfield, IL 60015 USA

PREMIER Pro Rx Logo
Made in Germany

Cyclophosphamide
for Injection, USP

1 gram/vial

Barcode

HA-80-02-323
USA

Each vial contains 1 g cyclophosphamide.

For IV Infusion Use:

Add 50 mL Sterile Water for Injection,

USP, and shake vigorously to dissolve

the drug.

For Direct Injection Use:Add 50 mL

0.9% Sodium Chloride Injection, USP,

and shake vigorously to dissolve

the drug.

Store vial at or below 25°C (77°F)

[ see USP Controlled Room Temperature].

DOSAGE:See accompanying literature

for directions for use. Should not be

prescribed without thorough knowledge

of dose, indications and toxicity as

contained in accompanying literature.

CYTOTOXIC AGENT

FOR SINGLE DOSE USE

STERILE, NON-PYROGENIC

FOR PARENTERAL USE

C
610

NDC 10019-944-01

C yclophosphamide
for Injection, USP

1 gram/vial

Rx only

MUST BE DILUTED

FOR IV INFUSION

OR DIRECT INJECTION USE

1 Single Dose Vial

Baxter Logo
Manufactured by
Baxter Healthcare Corporation
Deerfield, IL 60015 USA

PremierProRx is a trademark of

Premier Healthcare Alliance, L.P.,
used under license.
Made in Germany

LOT/EXP:

2638B5160

Barcode

NDC 10019-944-01

C yclophosphamide
for Injection, USP

1 gram/vial

Rx only

MUST BE DILUTED

FOR IV INFUSION

OR DIRECT INJECTION USE

1 Single Dose Vial

Baxter Logo
Manufactured by
Baxter Healthcare Corporation
Deerfield, IL 60015 USA

PremierProRx is a trademark of

Premier Healthcare Alliance, L.P.,
used under license.
Made in Germany

NDC 10019-945-10

C yclophosphamide
for Injection, USP

2 gram/vial

CYTOTOXIC AGENT

FOR SINGLE DOSE USE
STERILE, NON-PYROGENIC
FOR PARENTERAL USE

Rx only

Baxter Logo
Manufactured by Baxter Healthcare Corporation
Deerfield, IL 60015 USA

PREMIER Pro Rx Logo
Made in Germany

LOT/EXP:

Each vial contains 2 g cyclophosphamide.

For IV Infusion Use:Add 100 mL

Sterile Water for Injection, USP, and shake

vigorously to dissolve the drug.

For Direct Injection Use:Add 100 mL

0.9% Sodium Chloride Injection, USP, and

shake vigorously to dissolve the drug.

See insert for indications and dosage

schedule. Store vial at or below 25°C (77°F)

[see USP Controlled Room Temperature].

Bar Code
(01)00310019945101

USA HA-65-01-639 C924

NDC 10019-945-01

C yclophosphamide
for Injection, USP

2 gram/vial

Rx only

MUST BE DILUTED

FOR IV INFUSION

OR DIRECT INJECTION USE

1 Single Dose Vial

Baxter Logo
Manufactured by
Baxter Healthcare Corporation
Deerfield, IL 60015 USA

PREMIER Pro Rx Logo
Made in Germany

C yclophosphamide
for Injection, USP

2 gram/vial

Barcode

HA-80-02-324
USA

Each vial contains 2 g cyclophosphamide.

For IV Infusion Use:Add 100 mL Sterile Water
for Injection, USP, and shake vigorously to
dissolve the drug.

For Direct Injection Use:Add 100 mL

0.9% Sodium Chloride Injection, USP,

and shake vigorously to dissolve the drug.

Store vial at or below 25°C (77°F)

[ see USP Controlled Room Temperature].

DOSAGE:See accompanying literature

for directions for use. Should not be prescribed
without thorough knowledge of dose,
indications and toxicity as contained in
accompanying literature.

CYTOTOXIC AGENT

FOR SINGLE DOSE USE

STERILE, NON-PYROGENIC

FOR PARENTERAL USE

C
611

NDC 10019-945-01

C yclophosphamide
for Injection, USP

2 gram/vial

Rx only

MUST BE DILUTED

FOR IV INFUSION

OR DIRECT INJECTION USE

1 Single Dose Vial

Baxter Logo
Manufactured by
Baxter Healthcare Corporation
Deerfield, IL 60015 USA

PremierProRx is a trademark of

Premier Healthcare Alliance, L.P.,
used under license.
Made in Germany

LOT/EXP:

2638B5161

Barcode

NDC 10019-945-01

C yclophosphamide
for Injection, USP

2 gram/vial

Rx only

MUST BE DILUTED

FOR IV INFUSION

OR DIRECT INJECTION USE

1 Single Dose Vial

Baxter Logo
Manufactured by
Baxter Healthcare Corporation

Deerfield, IL 60015 USA

PremierProRx is a trademark of

Premier Healthcare Alliance, L.P.,
used under license.
Made in Germany